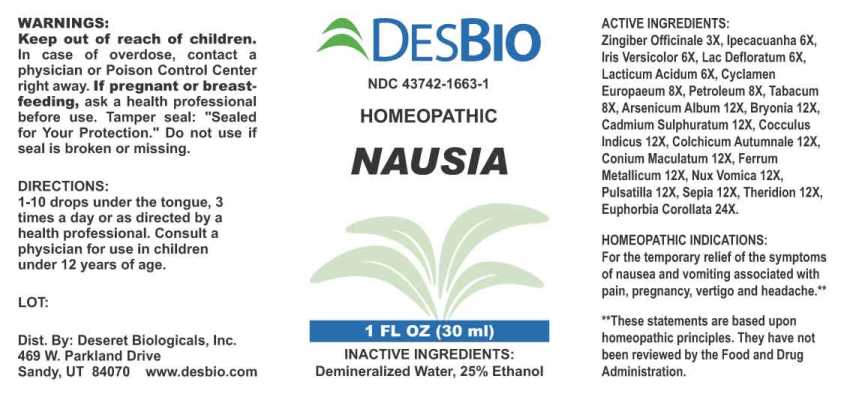 DRUG LABEL: Nausia
NDC: 43742-1663 | Form: LIQUID
Manufacturer: Deseret Biologicals, Inc.
Category: homeopathic | Type: HUMAN OTC DRUG LABEL
Date: 20240911

ACTIVE INGREDIENTS: GINGER 3 [hp_X]/1 mL; IPECAC 6 [hp_X]/1 mL; IRIS VERSICOLOR ROOT 6 [hp_X]/1 mL; SKIM MILK 6 [hp_X]/1 mL; LACTIC ACID, DL- 6 [hp_X]/1 mL; CYCLAMEN PURPURASCENS TUBER 8 [hp_X]/1 mL; KEROSENE 8 [hp_X]/1 mL; TOBACCO LEAF 8 [hp_X]/1 mL; ARSENIC TRIOXIDE 12 [hp_X]/1 mL; BRYONIA ALBA ROOT 12 [hp_X]/1 mL; CADMIUM SULFIDE 12 [hp_X]/1 mL; ANAMIRTA COCCULUS SEED 12 [hp_X]/1 mL; COLCHICUM AUTUMNALE BULB 12 [hp_X]/1 mL; CONIUM MACULATUM FLOWERING TOP 12 [hp_X]/1 mL; IRON 12 [hp_X]/1 mL; STRYCHNOS NUX-VOMICA SEED 12 [hp_X]/1 mL; PULSATILLA PRATENSIS WHOLE 12 [hp_X]/1 mL; SEPIA OFFICINALIS JUICE 12 [hp_X]/1 mL; THERIDION CURASSAVICUM 12 [hp_X]/1 mL; EUPHORBIA COROLLATA ROOT 24 [hp_X]/1 mL
INACTIVE INGREDIENTS: WATER; ALCOHOL

DRUG FACTS:

ACTIVE INGREDIENTS:

Zingiber Officinale 3X, Ipecacuanha 6X, Iris Versicolor 6X, Lac Defloratum 6X, Lacticum Acidum 6X, Cyclamen Europaeum 8X, Petroleum 8X, Tabacum 8X, Arsenicum Album 12X, Bryonia (Alba) 12X, Cadmium Sulphuratum 12X, Cocculus Indicus 12X, Colchicum Autumnale 12X, Conium Maculatum 12X, Ferrum Metallicum 12X, Nux Vomica 12X, Pulsatilla (Pratensis) 12X, Sepia 12X, Theridion 12X, Euphorbia Corollata 24X.

HOMEOPATHIC INDICATIONS:

For the temporary relief of the symptoms of nausea and vomiting associated with pain, pregnancy, vertigo and headache.**

**These statements are based upon homeopathic principles. They have not been reviewed by the Food and Drug Administration.

WARNINGS:

Keep out of reach of children. In case of overdose, contact a physician or Poison Control Center right away.
If pregnant or breast-feeding, ask a health professional before use.
Tamper seal: "Sealed for Your Protection." Do not use if seal is broken or missing.

Keep out of reach of children. In case of overdose, contact physician or Poison Control Center right away.

DIRECTIONS:

1-10 drops under the tongue, 3 times a day or as directed by a health professional. Consult a physician for use in children under 12 years of age.

HOMEOPATHIC INDICATIONS:

For the temporary relief of the symptoms of nausea and vomiting associated with pain, pregnancy, vertigo and headache.**

**These statements are based upon homeopathic principles. They have not been reviewed by the Food and Drug Administration.

INACTIVE INGREDIENTS:

Demineralized Water, 25% Ethanol

QUESTIONS:

Dist. By: Deseret Biologicals, Inc.
469 W. Parkland Drive
Sandy, UT 84070 www.desbio.com

PACKAGE LABEL DISPLAY:

DESBIO
NDC 43742-1663-1
HOMEOPATHIC
NAUSIA
1 FL OZ (30 ml)